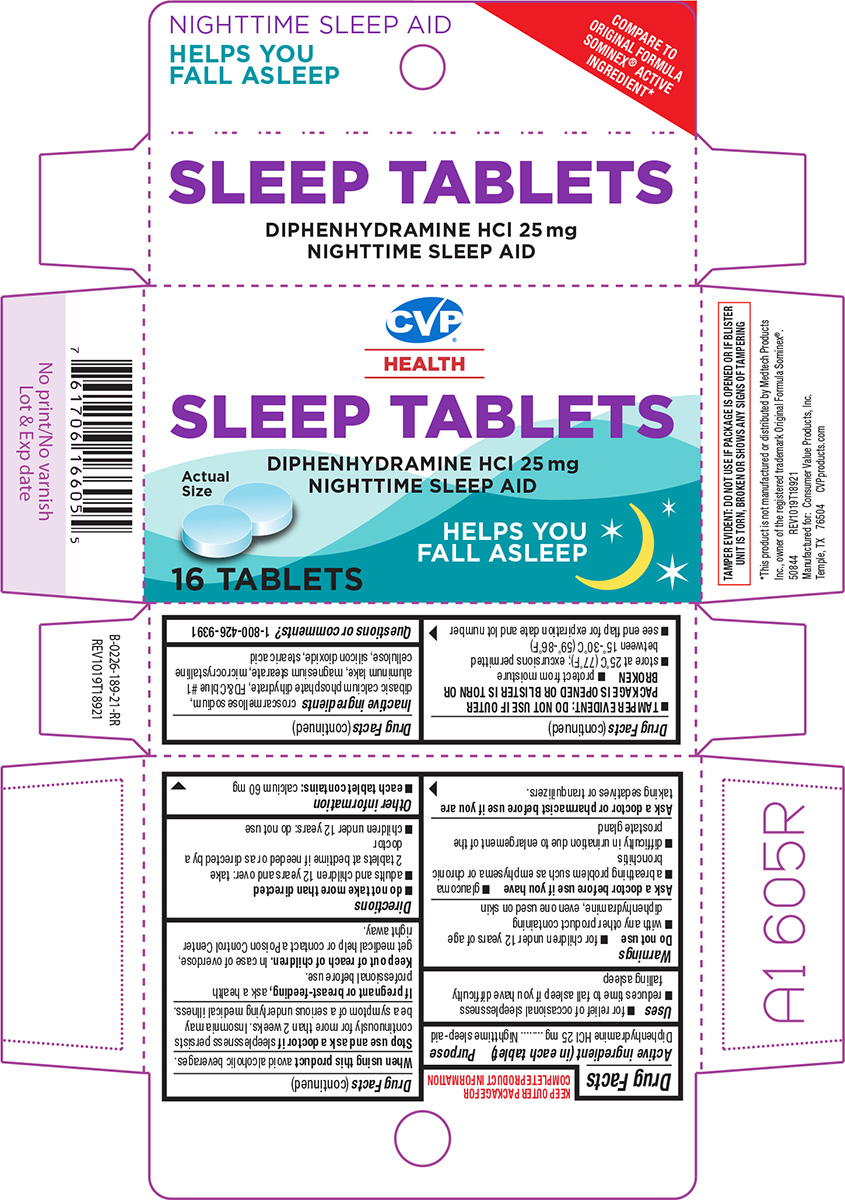 DRUG LABEL: Sleep
NDC: 57243-189 | Form: TABLET
Manufacturer: Salado Sales, Inc.
Category: otc | Type: HUMAN OTC DRUG LABEL
Date: 20251124

ACTIVE INGREDIENTS: DIPHENHYDRAMINE HYDROCHLORIDE 25 mg/1 1
INACTIVE INGREDIENTS: CROSCARMELLOSE SODIUM; DIBASIC CALCIUM PHOSPHATE DIHYDRATE; FD&C BLUE NO. 1 ALUMINUM LAKE; MAGNESIUM STEARATE; MICROCRYSTALLINE CELLULOSE; SILICON DIOXIDE; STEARIC ACID

CVP 44-189

Active ingredient (in each tablet)

Diphenhydramine HCl 25 mg

Purpose

Nighttime sleep-aid

Uses

- for relief of occasional sleeplessness
- reduces time to fall asleep if you have difficulty falling asleep

Warnings

Do not use

- for children under 12 years of age
- with any other product containing diphenhydramine, even one used on skin

Ask a doctor before use if you have

- glaucoma
- a breathing problem such as emphysema or chronic bronchitis
- difficulty in urination due to enlargement of the prostate gland

Ask a doctor or pharmacist before use if you are

taking sedatives or tranquilizers.

When using this product

avoid alcoholic beverages.

Stop use and ask a doctor if

sleeplessness persists continuously for more than 2 weeks. Insomnia may be a symptom of a serious underlying medical illness.

If pregnant or breast-feeding,

ask a health professional before use.

Keep out of reach of children.

In case of overdose, get medical help or contact a Poison Control Center right away.

Directions

- do not take more than directed
- adults and children 12 years and over: take 2 tablets at bedtime if needed or as directed by a doctor
- children under 12 years: do not use

Other information

- each tablet contains: calcium 60 mg
- TAMPER EVIDENT: DO NOT USE IF OUTER PACKAGE IS OPENED OR BLISTER IS TORN OR BROKEN
- protect from moisture
- store at 25°C (77°F); excursions permitted between 15°-30°C (59°-86°F)
- see end flap for expiration date and lot number

Inactive ingredients

croscarmellose sodium, dibasic calcium phosphate dihydrate, FD&C blue #1 aluminum lake, magnesium stearate, microcrystalline cellulose, silicon dioxide, stearic acid

Questions or comments?

1-800-426-9391

Principal Display Panel

COMPARE TO
ORIGINAL FORMULA
SOMINEX® ACTIVE
INGREDIENT*

CVP®
HEALTH

SLEEP TABLETS

DIPHENHYDRAMINE HCl 25 mg
NIGHTTIME SLEEP AID

Actual Size

16 TABLETS

HELPS YOU
FALL ASLEEP

TAMPER EVIDENT: DO NOT USE IF PACKAGE IS OPENED OR IF BLISTER
UNIT IS TORN, BROKEN OR SHOWS ANY SIGNS OF TAMPERING

*This product is not manufactured or distributed by Medtech Products
Inc., owner of the registered trademark Original Formula Sominex®.
50844 REV1019T18921

Manufactured for: Consumer Value Products, Inc.
Temple, TX 76504 CVPproducts.com

CVP 44-189